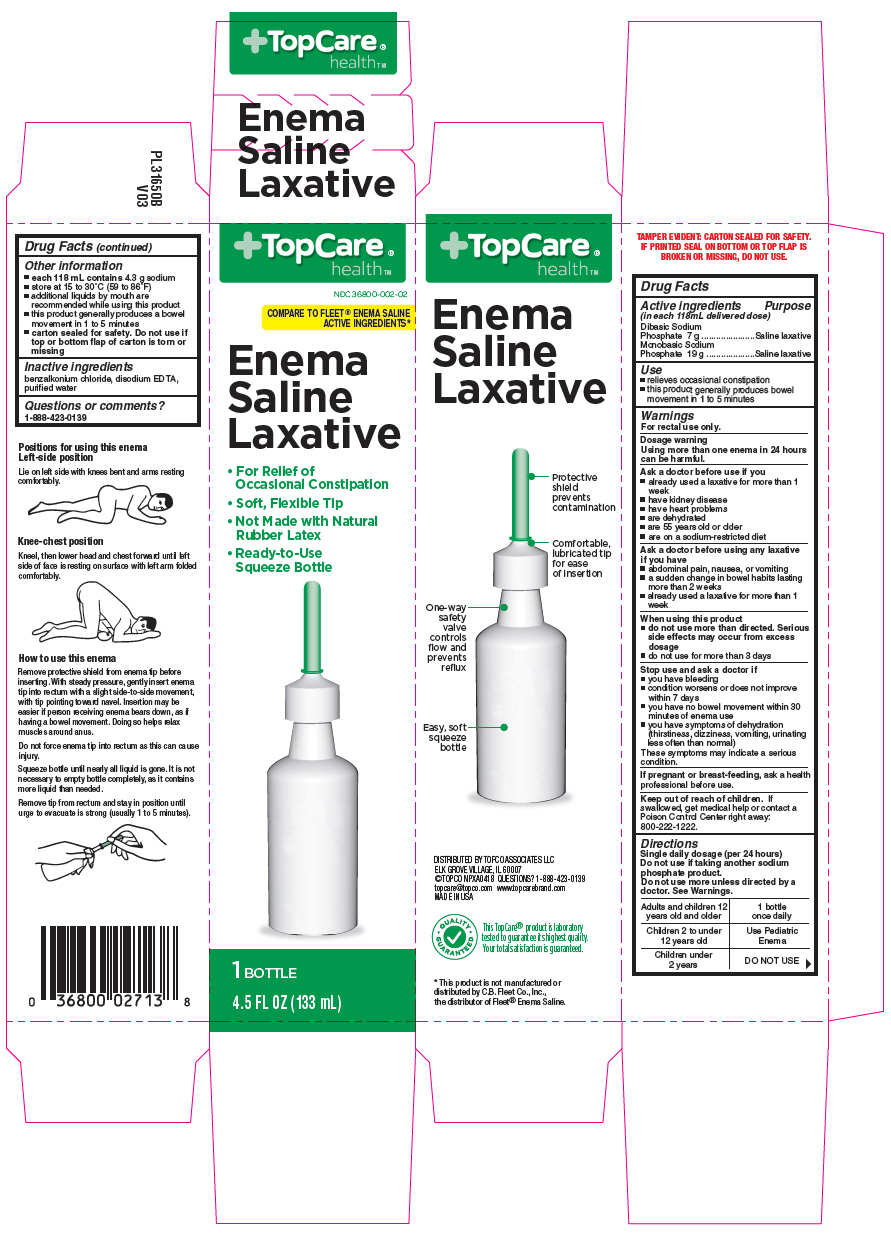 DRUG LABEL: topcare enema
NDC: 36800-002 | Form: ENEMA
Manufacturer: Topco Associates LLC
Category: otc | Type: HUMAN OTC DRUG LABEL
Date: 20190118

ACTIVE INGREDIENTS: SODIUM PHOSPHATE, DIBASIC, UNSPECIFIED FORM 7 g/118 mL; SODIUM PHOSPHATE, MONOBASIC, UNSPECIFIED FORM 19 g/118 mL
INACTIVE INGREDIENTS: BENZALKONIUM CHLORIDE; EDETATE DISODIUM; WATER

TOPCARE® ENEMA SALINE LAXATIVE
LAXATIVE

Drug Facts

ACTIVE INGREDIENT

Active ingredients (in each 118mL delivered dose) | Purpose
Dibasic Sodium Phosphate 7 g | Saline laxative
Monobasic Sodium Phosphate 19 g | Saline laxative

Use

- relieves occasional constipation
- this product generally produces bowel movement in 1 to 5 minutes

Warnings

For rectal use only.

Dosage warning

Using more than one enema in 24 hours can be harmful.

Ask a doctor before use if you

- already used a laxative for more than 1 week
- have kidney disease
- have heart problems
- are dehydrated
- are 55 years old or older
- are on a sodium-restricted diet

Ask a doctor before using any laxative if you have

- abdominal pain, nausea, or vomiting
- a sudden change in bowel habits lasting more than 2 weeks
- already used a laxative for more than 1 week

When using this product

- do not use more than directed. Serious side effects may occur from excess dosage
- do not use for more than 3 days

Stop use and ask a doctor if

- you have bleeding
- condition worsens or does not improve within 7 days
- you have no bowel movement within 30 minutes of enema use
- you have symptoms of dehydration (thirstiness, dizziness, vomiting, urinating less often than normal)

These symptoms may indicate a serious condition.

PREGNANCY OR BREAST FEEDING

If pregnant or breast-feeding, ask a health professional before use.

Keep out of reach of children. If swallowed, get medical help or contact a Poison Control Center right away: 800-222-1222.

Directions

Single daily dosage (per 24 hours)

Do not use if taking another sodium phosphate product.

Do not use more unless directed by a doctor. See Warnings.

Adults and children 12 years old and older | 1 bottle once daily
Children 2 to under 12 years old | Use Pediatric Enema
Children under 2 years | DO NOT USE

Other information

- each 118 mL contains 4.3 g sodium
- store at 15 to 30°C (59 to 86°F)
- additional liquids by mouth are recommended while using this product
- this product generally produces a bowel movement in 1 to 5 minutes
- carton sealed for safety. Do not use if top or bottom flap of carton is torn or missing

Inactive ingredients

benzalkonium chloride, disodium EDTA, purified water

Questions or comments?

1-888-423-0139

DISTRIBUTED BY TOPCO ASSOCIATES LLC
ELK GROVE VILLAGE, IL 60007

PRINCIPAL DISPLAY PANEL - 133 mL Bottle Carton

TopCare®
health™

NDC 36800-002-02

COMPARE TO FLEET® ENEMA SALINE
ACTIVE INGREDIENTS*

Enema
Saline
Laxative

- For Relief of
  Occasional Constipation
- Soft, Flexible Tip
- Not Made with Natural
  Rubber Latex
- Ready-to-Use
  Squeeze Bottle

1 BOTTLE

4.5 FL OZ (133 mL)